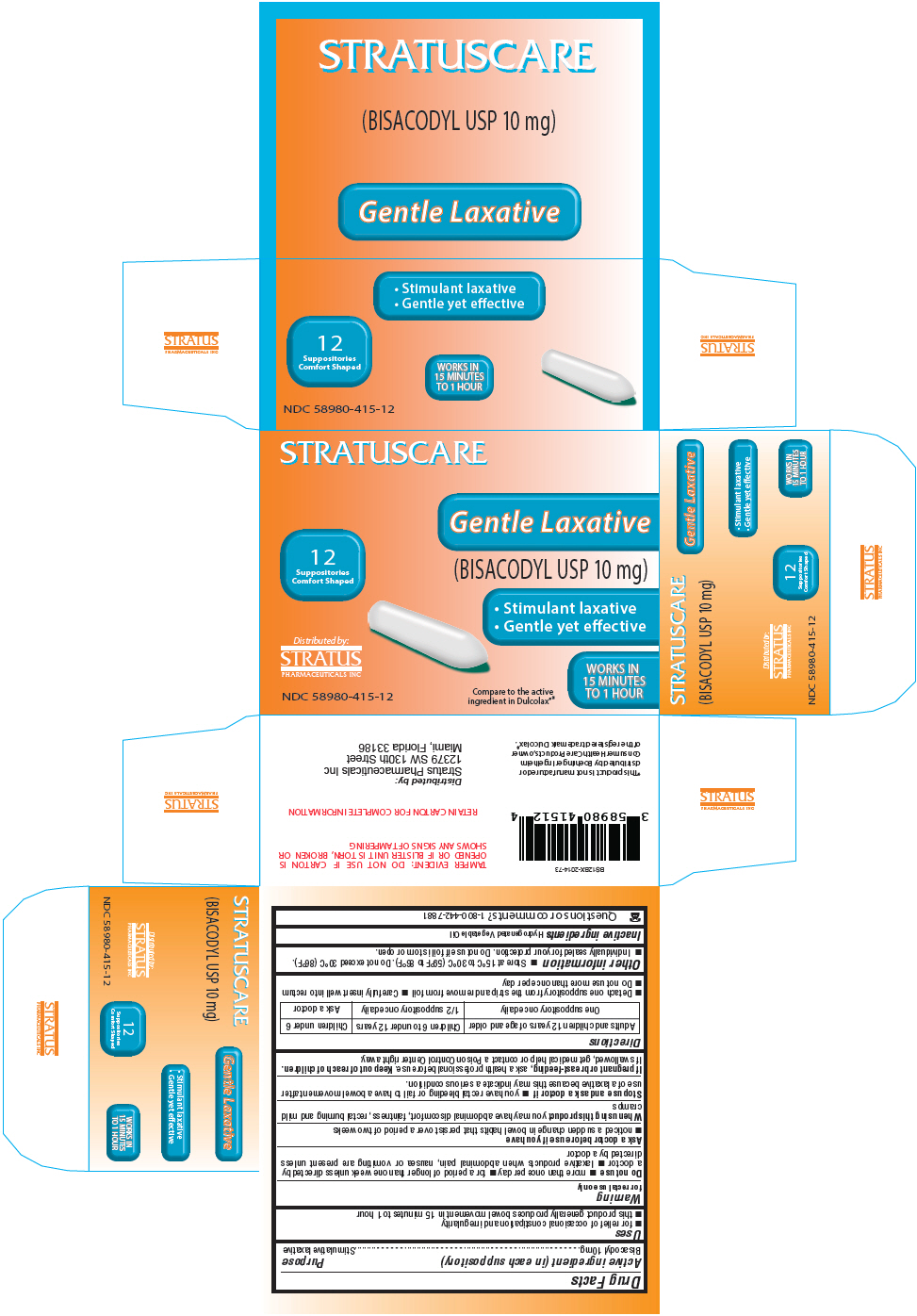 DRUG LABEL: Stratuscare Bisacodyl
NDC: 58980-415 | Form: SUPPOSITORY
Manufacturer: Stratus Pharmaceuticals
Category: otc | Type: HUMAN OTC DRUG LABEL
Date: 20250417

ACTIVE INGREDIENTS: Bisacodyl 10 mg/1 1
INACTIVE INGREDIENTS: HYDROGENATED SOYBEAN OIL

BISACODYL USP

Drug Facts

Active ingredient (in each suppository)

Bisacodyl 10mg

Purpose

Stimulative laxative

Uses

- for relief of occasional constipation and irregularity
- this product generally produces bowel movement in 15 minutes to 1 hour

Warning

for rectal use only

Do not use

- more than once per day
- for a period of longer than one week unless directed by a doctor
- laxative products when abdominal pain, nausea or vomiting are present unless directed by a doctor

Ask a doctor before use if you have

- noticed a sudden change in bowel habits that persist over a period of two weeks

When using this product you may have abdominal discomfort, faintness, rectal burning and mild cramps

Stop use and ask a doctor if

- you have rectal bleeding or fail to have a bowel movement after use of a laxative because this may indicate a serious condition.

PREGNANCY OR BREAST FEEDING

If pregnant or breast-feeding, ask a health professional before use.

Keep out of reach of children. If swallowed, get medical help or contact a Poison Control Center right away.

Directions

Adults and children 12 years of age and older | Children 6 to under 12 years | Children under 6
One suppository once daily | 1/2 suppository once daily | Ask a doctor

- Detach one suppository from the strip and remove from foil
- Carefully insert well into rectum
- Do not use more than once per day

Other information

- Store at 15°C to 30°C (59°F to 86°F). Do not exceed 30°C (86°F).
- Individually sealed for your protection. Do not use if foil is torn or open.

Inactive ingredients

Hydrogenated Vegetable Oil

Questions or comments?

1-800-442-7881

Distributed by:
Stratus Pharmaceuticals Inc
12379 SW 130th Street
Miami, Florida 33186

PRINCIPAL DISPLAY PANEL - 10 mg Blister Pack Box

STRATUSCARE

12
Suppositories
Comfort Shaped

Distributed by:
STRATUS
PHARMACEUTICALS INC

NDC 58980-415-12

Gentle Laxative
(BISACODYL USP 10 mg)

- Stimulant laxative
- Gentle yet effective

WORKS IN
15 MINUTES
TO 1 HOUR

Compare to the active
ingredient in Dulcolax®*